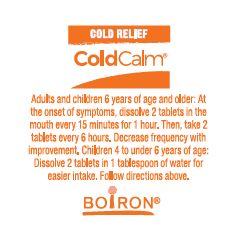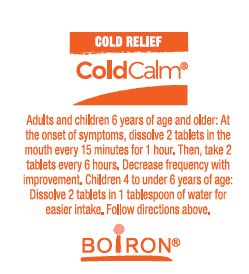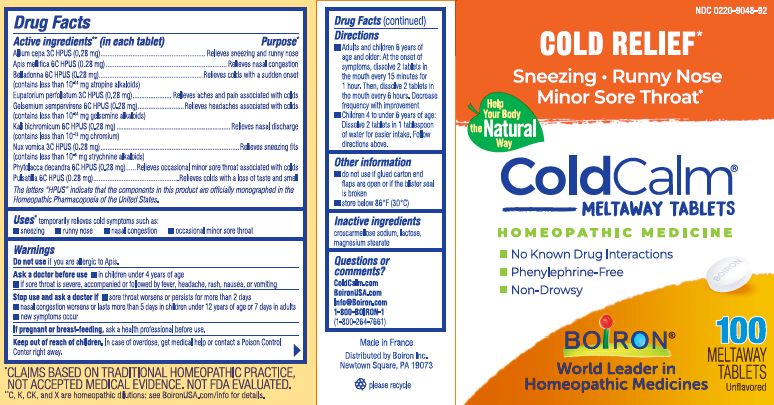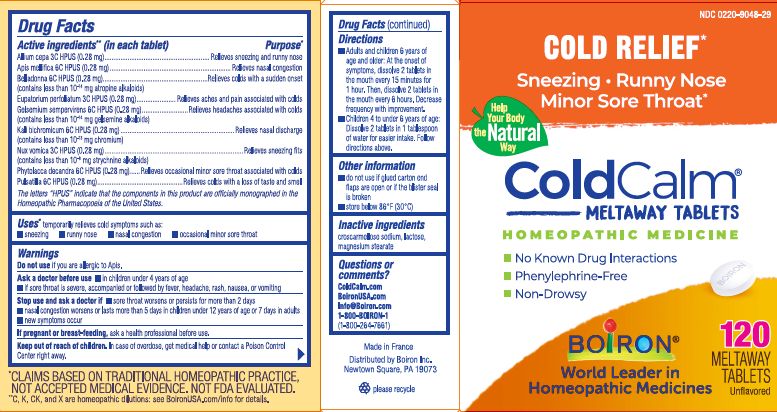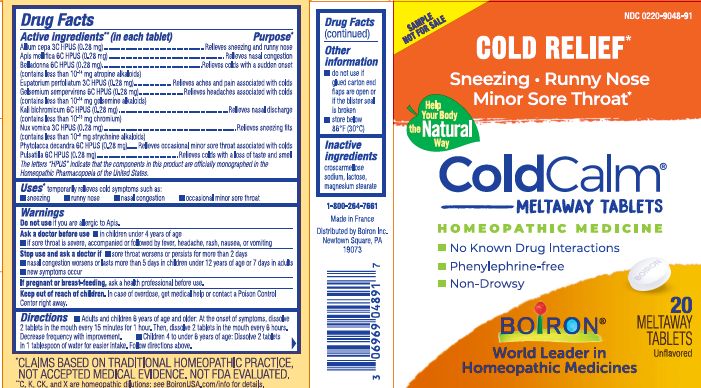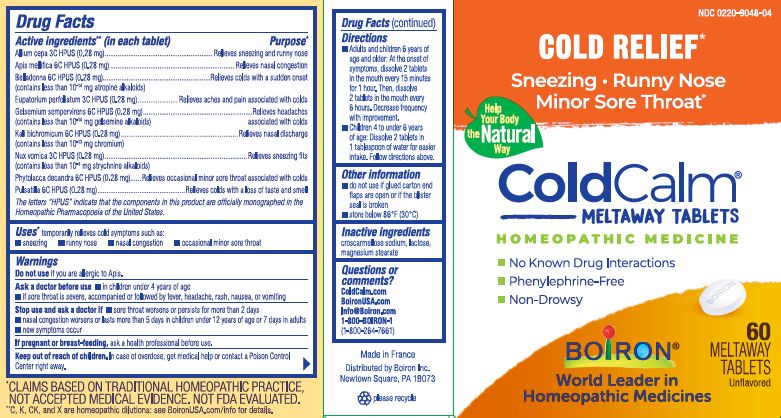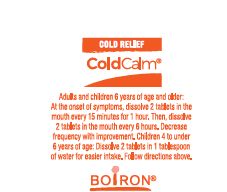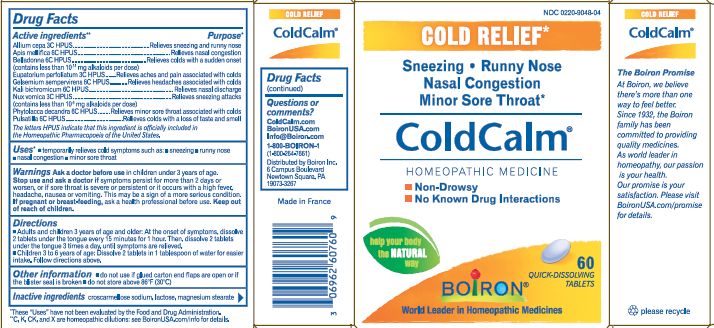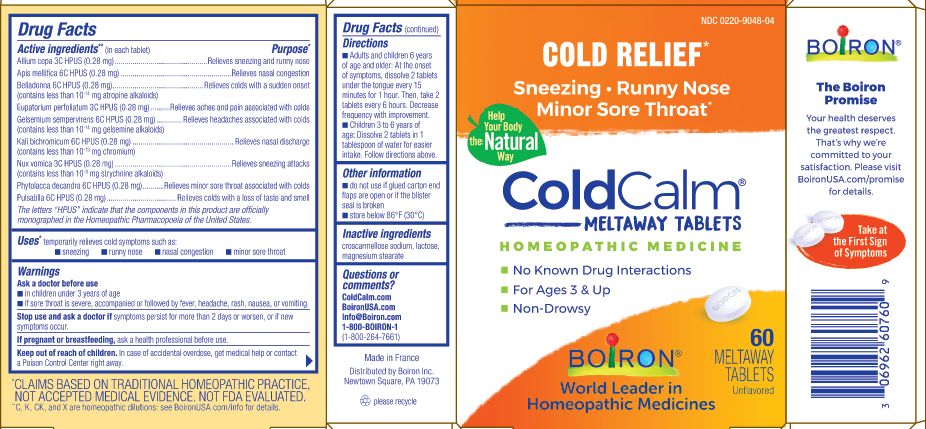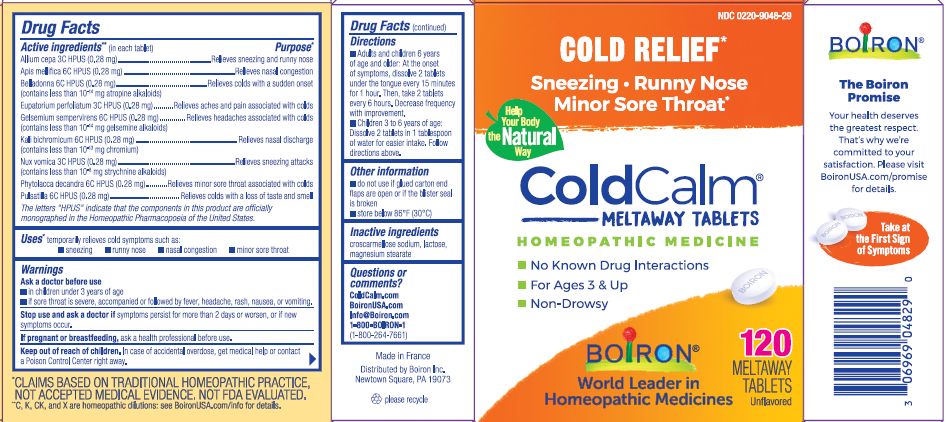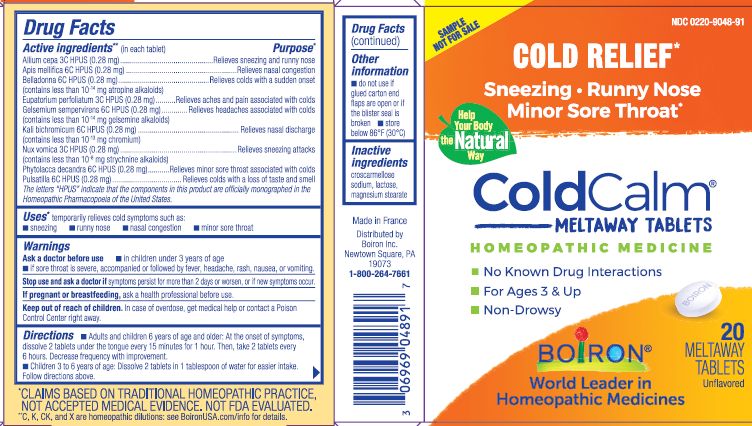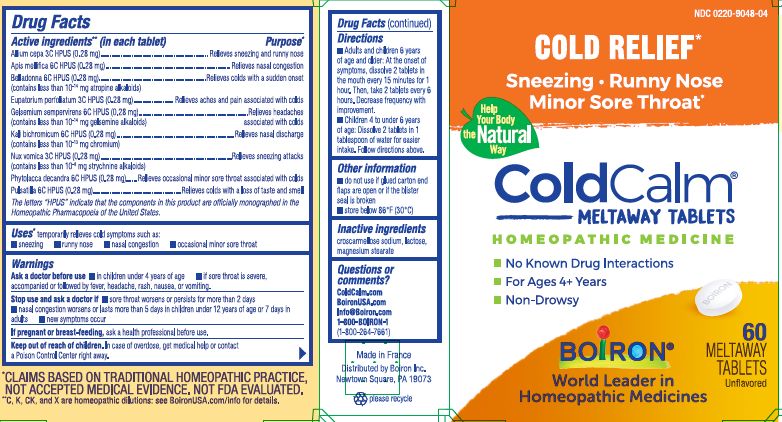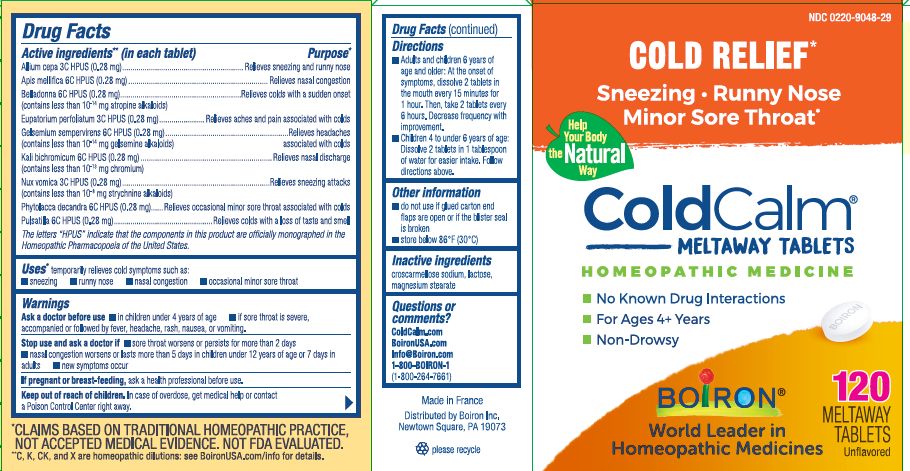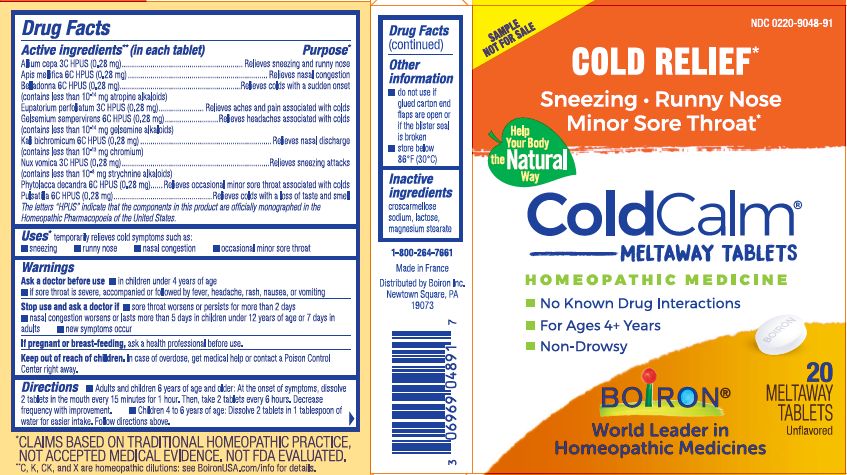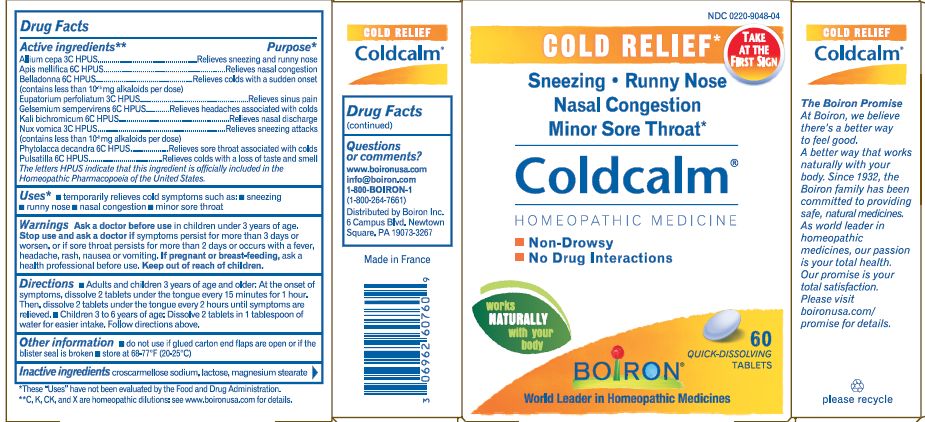 DRUG LABEL: Coldcalm
NDC: 0220-9048 | Form: TABLET
Manufacturer: Laboratoires Boiron
Category: homeopathic | Type: HUMAN OTC DRUG LABEL
Date: 20250401

ACTIVE INGREDIENTS: ONION 3 [hp_C]/1 1; APIS MELLIFERA 6 [hp_C]/1 1; ATROPA BELLADONNA 6 [hp_C]/1 1; EUPATORIUM PERFOLIATUM FLOWERING TOP 3 [hp_C]/1 1; GELSEMIUM SEMPERVIRENS ROOT 6 [hp_C]/1 1; DICHROMATE ION 6 [hp_C]/1 1; STRYCHNOS NUX-VOMICA SEED 3 [hp_C]/1 1; PHYTOLACCA AMERICANA ROOT 6 [hp_C]/1 1; PULSATILLA VULGARIS 6 [hp_C]/1 1
INACTIVE INGREDIENTS: CROSCARMELLOSE SODIUM; LACTOSE; MAGNESIUM STEARATE

Coldcalm

Active ingredients** (in each tablet)

Allium cepa 3C HPUS (0.28 mg)

Apis mellifica 6C HPUS (0.28 mg)

Belladonna 6C HPUS (0.28 mg) (contains less than 10^-14 mg atropine alkaloids)

Eupatorium perfoliatum 3C HPUS (0.28 mg)

Gelsemium sempervirens 6C HPUS (0.28 mg) (contains less than 10^-14 gelsemine alkaloids)

Kali bichromicum 6C HPUS (0.28 mg) (contains less than 10^-13 mg chromium)

Nux vomica 3C HPUS (0.28 mg) (contains less than 10^-8 mg strychnine alkaloids)

Phytolacca decandra 6C HPUS (0.28 mg)

Pulsatilla 6C HPUS (0.28 mg)

The letters "HPUS" indicate that the components in this product are officially monographed in the Homeopathic Pharmacopoeia of the United States.

Purpose*

Allium cepa 3C HPUS ... Relieves sneezing and runny nose

Apis mellifica 6C HPUS ... Relieves nasal congestion

Belladonna 6C HPUS ... Relieves colds with a sudden onset

Eupatorium perfoliatum 3C HPUS ... Relieves aches and pain associated with colds

Gelsemium sempervirens 6C HPUS ... Relieves headaches associated with colds

Kali bichromicum 6C HPUS ... Relieves nasal discharge

Nux vomica 3C HPUS .... Relieves sneezing fits

Phytolacca decandra 6C HPUS ... Relieves occasional minor sore throat associated with colds

Pulsatilla 6C HPUS ... Relieves colds with a loss of taste and smell

Uses*

temporarily relieves cold symptoms such as:

- sneezing
- runny nose
- nasal congestion
- occasional minor sore throat

Do not use if you are allergic to Apis.

Ask a doctor before use

- in children under 4 years of age
- if sore throat is severe, accompanied or followed by fever, headache, rash, nausea, or vomiting

Stop use and ask a doctor if sore throat worsens or persists for more than 2 days

nasal congestion worsens or lasts more than 5 days in children under 12 years of age or 7 days in adults

new symptoms occur

PREGNANCY OR BREAST FEEDING

If pregnant or breast-feeding, ask a health professional before use.

Keep out of reach of children. In case of overdose, get medical help or contact a Poison Control Center right away.

Directions

- Adults and children 6 years of age and older: At the onset of symptoms, dissolve 2 tablets in mouth every 15 minutes for 1 hour. Then, dissolve 2 tablets every 6 hours. Decrease frequency with improvement.
- Children 4 to under 6 years of age: Dissolve 2 tablets in 1 tablespoon of water for easier intake. Follow directions above.

- do not use if glued carton end flaps are open or if the blister seal is broken
- store below 86° F (30° C)

Contains 20 meltaway tablets unflavored

Contains 60 meltaway tablets unflavored

Contains 100 meltway tablets unflavored

Contains 120 meltaway tablets unflavored

No Known Drug Interactions

Phenylephrine-free

Non-Drowsy

Cold Relief*

Sneezing, Runny Nose, Minor Sore Throat*

*CLAIMS BASED ON TRADITIONAL HOMEOPATHIC PRACTICE, NOT ACCEPTED MEDICAL EVIDENCE. NOT FDA EVALUATED.
*C,K,CK, and X are homeopathic dilutions: see BoironUSA.com/info for details.

INACTIVE INGREDIENT

croscarmellose sodium, lactose, magnesium stearate

Questions or comments
ColdCalm.com

BoironUSA.com

Info@Boiron.com

1-800-BOIRON-1

(1-800-264-7661)

Distributed by Boiron, Inc.

Newtown Square, PA 19073

Made in France